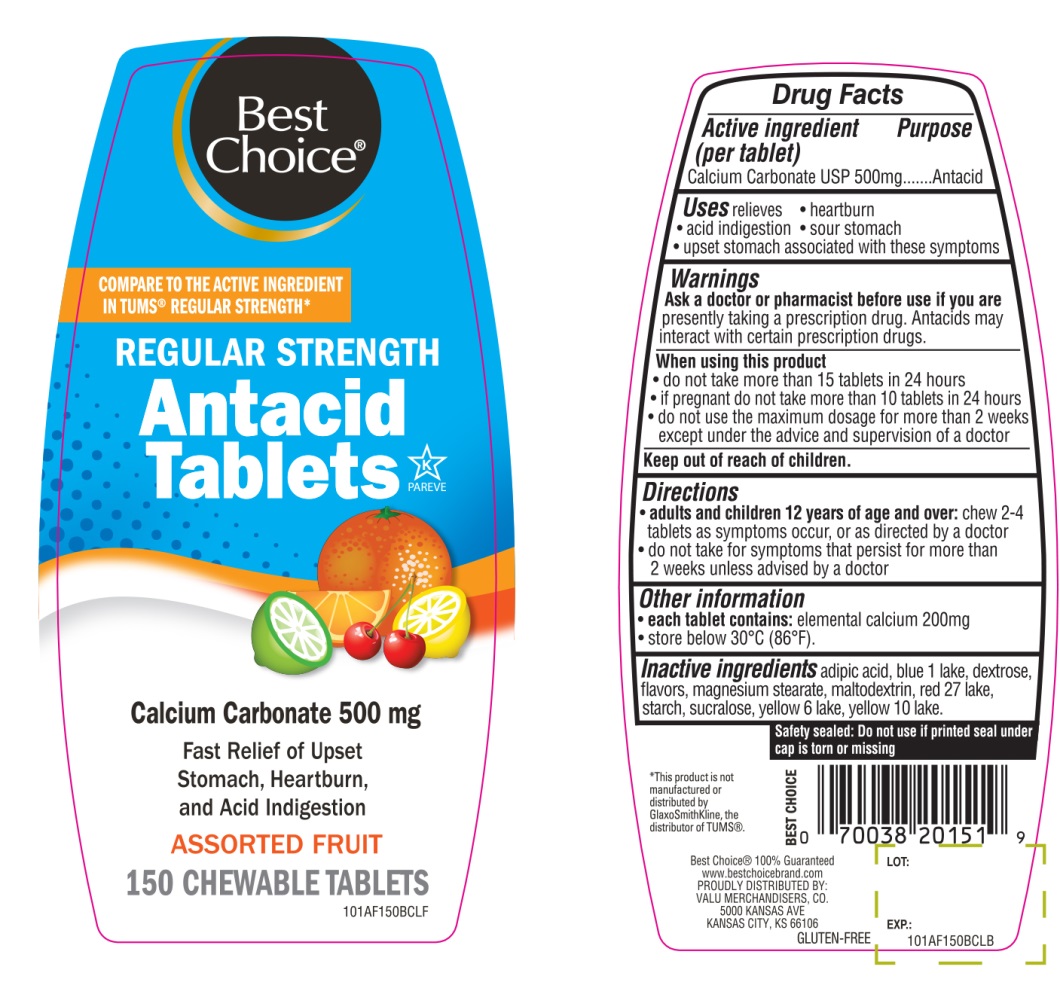 DRUG LABEL: Best Choice

NDC: 63941-010 | Form: TABLET, CHEWABLE
Manufacturer: BEST CHOICE (VALU MERCHANDISERS COMPANY)
Category: otc | Type: HUMAN OTC DRUG LABEL
Date: 20250715

ACTIVE INGREDIENTS: CALCIUM CARBONATE 500 mg/1 1
INACTIVE INGREDIENTS: ADIPIC ACID; FD&C BLUE NO. 1; DEXTROSE, UNSPECIFIED FORM; MAGNESIUM STEARATE; MALTODEXTRIN; D&C RED NO. 27; STARCH, CORN; SUCRALOSE; FD&C YELLOW NO. 6; D&C YELLOW NO. 10

Best Choice®Regular Strength Assorted Fruit Antacid Tablets

Active ingredient (per tablet)

Calcium Carbonate USP 500mg

Purpose

Antacid

Uses

relieves

- heartburn
- acid indigestion
- sour stomach
- upset stomach associated with these symptoms

Warnings

Ask a doctor or pharmacist before use if you arepresently taking a prescription drug. Antacids may interact with certain prescription drugs.

When using this product

- do not take more than 15 tablets in 24 hours
- If pregnant do not take more than10 tablets in 24 hours
- do not use the maximum dosage for more than 2 weeks except under the advice and supervision of a doctor.

Directions

- adults and children 12 years and over: chew 2-4 tablets as symptoms occur, or as directed by a doctor.
- do not take for symptoms that persist for more than 2 weeks unless advised by a doctor.

Other information

- each tablet contains:elemental calcium 200 mg
- store below 30°C (86°F)

Safety Sealed: Do not use if printed seal under cap is torn or missing.

Inactive ingredients

adipic acid, blue 1 lake, dextrose, flavors, magnesium stearate, maltodextrin, red 27 lake, starch, sucralose, yellow 6 lake, yellow 10 lake.

Questions or comments?

1-866-467-2748

Package/Label Principal Display Panel

NDC 63941-010-50

Best Choice®

COMPARE TO THE ACTIVE INGREDIENT IN TUMS®REGULAR STRENGTH*

REGULAR STRENGTH

Antacid Tablets

Calcium Carbonate 500 mg

Fast Relief of Upset Stomach, Heartburn and Acid Indigestion

ASSORTED FRUIT

150 CHEWABLE TABLETS

GLUTEN-FREE

K PAREVE

Best Choice®100% Guaranteed www.bestchoicebrand.com

PROUDLY DISTRIBUTED BY:

VALU MERCHANDISERS, CO.

5000 KANSAS AVE

KANSAS CITY, KS 66106

*This product is not manufactured or distributed by GlaxoSmithKline LLC, the distributor of TUMS®.